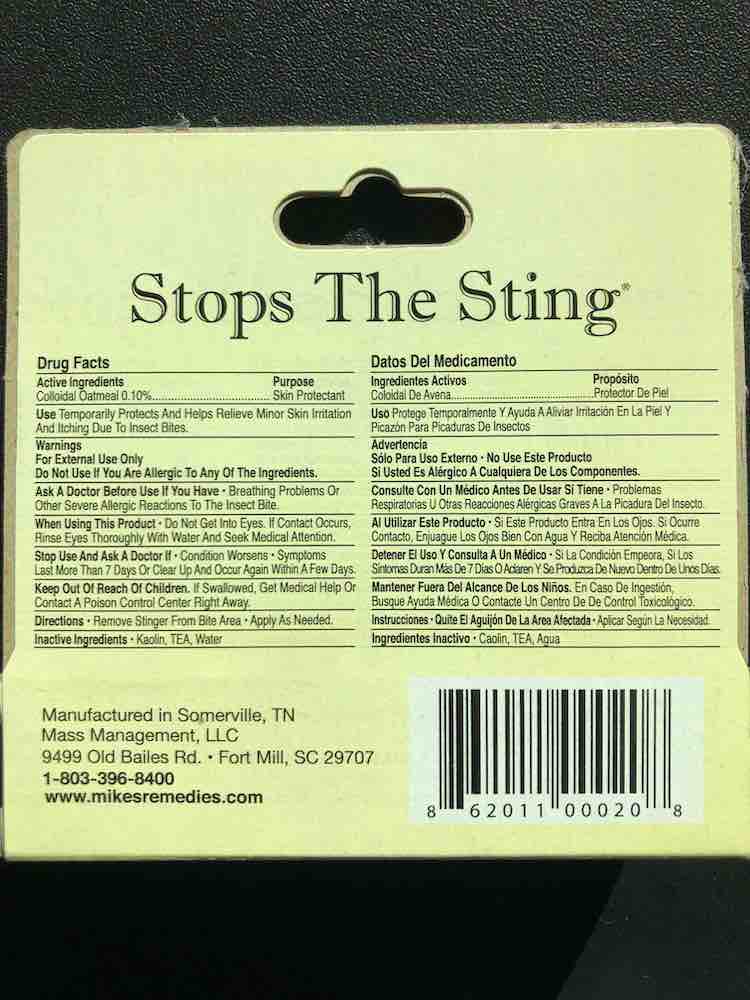 DRUG LABEL: Stops the Sting
NDC: 81937-0001 | Form: OINTMENT
Manufacturer: Mass Management LLC
Category: otc | Type: HUMAN OTC DRUG LABEL
Date: 20220210

ACTIVE INGREDIENTS: OATMEAL 0.1 g/100 g
INACTIVE INGREDIENTS: KAOLIN; TROLAMINE; WATER

Stops the Sting .37 oz Tube